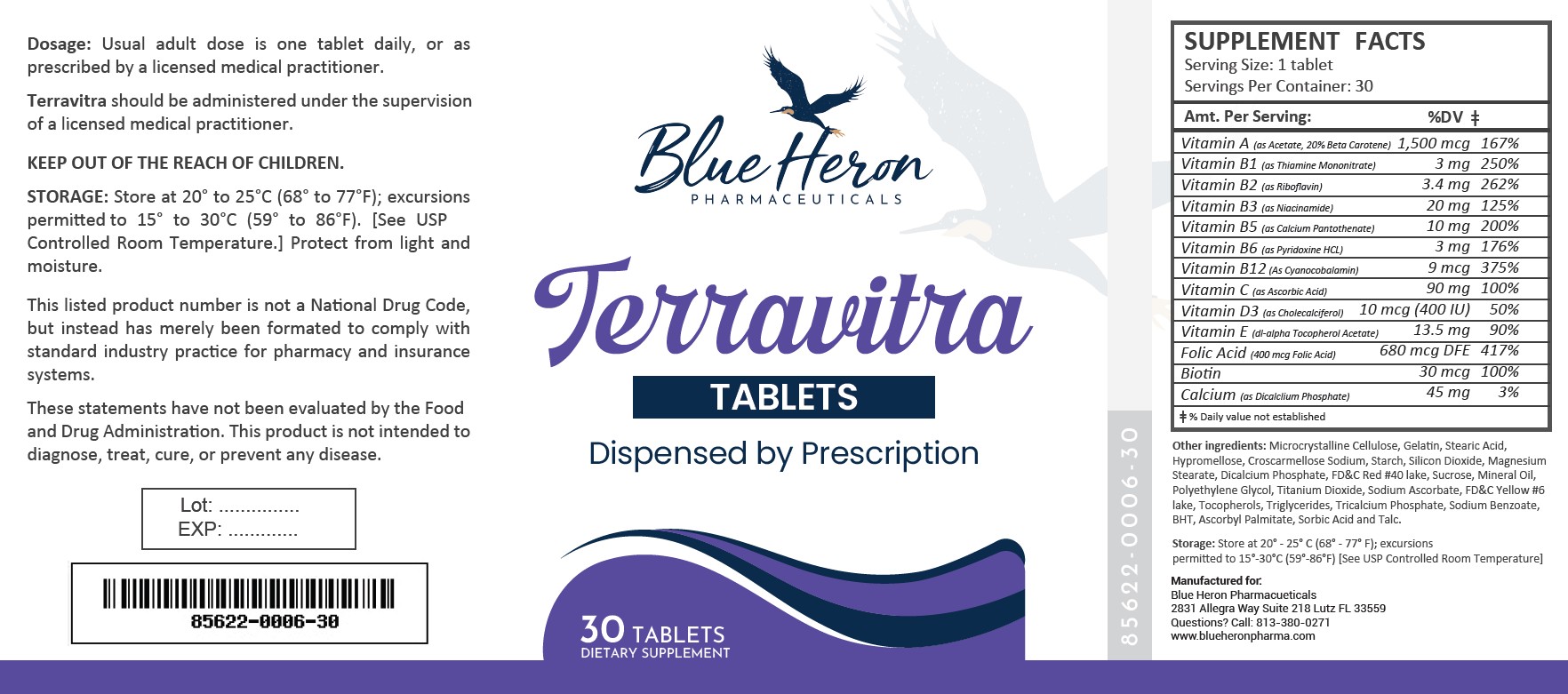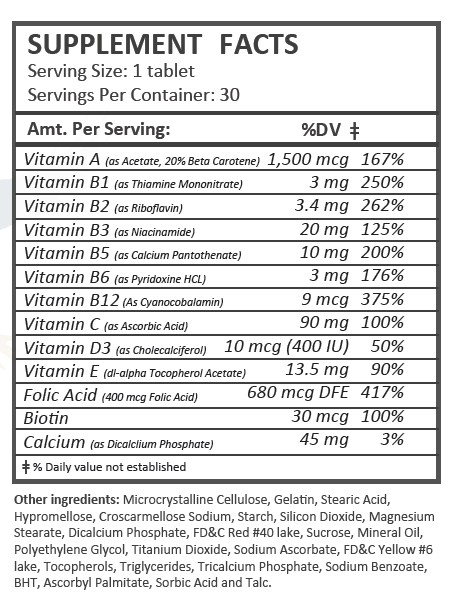 DRUG LABEL: Terravitra
NDC: 85622-006 | Form: TABLET
Manufacturer: Blue Heron Pharmaceuticals, LLC
Category: other | Type: Dietary Supplement
Date: 20260116

ACTIVE INGREDIENTS: ASCORBIC ACID 90 mg/1 1; BIOTIN 30 ug/1 1; CHOLECALCIFEROL 10 ug/1 1; CYANOCOBALAMIN 9 ug/1 1; FOLIC ACID 400 ug/1 1; NIACINAMIDE 20 mg/1 1; CALCIUM PANTOTHENATE 10 mg/1 1; PYRIDOXINE HYDROCHLORIDE 3 mg/1 1; VITAMIN A ACETATE 1500 ug/1 1; RIBOFLAVIN 3.4 mg/1 1; THIAMINE MONONITRATE 3 mg/1 1; .ALPHA.-TOCOPHEROL ACETATE, DL- 13.5 mg/1 1; CALCIUM 45 mg/1 1

Terravitra

Health Claim Section:

Vitrax Multivitamin

Dispensed by Prescription

Description:

Terravitra Tablets are supplied as brown, oblong tablets dispensed in plastic bottles of 30 ct.

85622-0006-30

Reserved for Professional Recommendation

Terravitra tablets are an orally administered prescription vitamin to provide significant amounts of Vitamins B6, B12, C, D3, E, riboflavin, niacinamide, thiamine monoitrate, and folate to supplement the diet, and to help assure that nutritional deficiencies of these vitamines will not develop.

Terravitra Tablets should be administered under the supervision of a licensed medical practitioner.

This listed product is not a National Drug Code, but instead has merely been formatted to comply with standard industry practice for pharmacy and insurance computer systems.

These statements have not been evaluated by the Food and Drug Administration. This product is not intended to diagnose, treat, cure or prevent any disease.

All prescriptions using this product shall be pursuant to state statutes as applicable. This is not an Orange Book product. This product may be administered only under a physician’s supervision. There are no implied or explicit claims on therapeutic equivalence.

Manufactured for:

Blue Heron Pharmaceuticals

Lutz, FL 33559

Warnings:

This product is contraindicated in patients with a known hypersensitivity to any of the ingredients.

Terravitra Tablets should only be used under the direction and supervision of a licensed medical practitioner. Use with caution in patients that may have a medical condition, are pregnant, lactating, trying to conceive, under the age of 18, or taking medications.

These statements have not been evaluated by the Food and Drug Administration. This product is not intended to diagnose, treat, cure, or prevent any disease.

Dosage and Administration:

Usual adult dose is one tablet daily, or as prescribed by a licensed medical practitioner.

Precautions:

CONTRAINDICATIONS
This product is contraindicated in patients with known hypersensitivity to any of the ingredients.

PRECAUTIONS
This product is contraindicated in patients with a known hypersensitivity to any of the ingredients.

ADVERSE REACTIONS
Allergic sensitizations have been reported following oral administration of folic acid. Consult your physician immediately if adverse side effects occur.

KEEP OUT OF THE REACH OF CHILDREN.

Storage:

Store at 20° to 25°C (68° to 77°F); excursions permitted to 15° to 30°C (59° to 86°F).